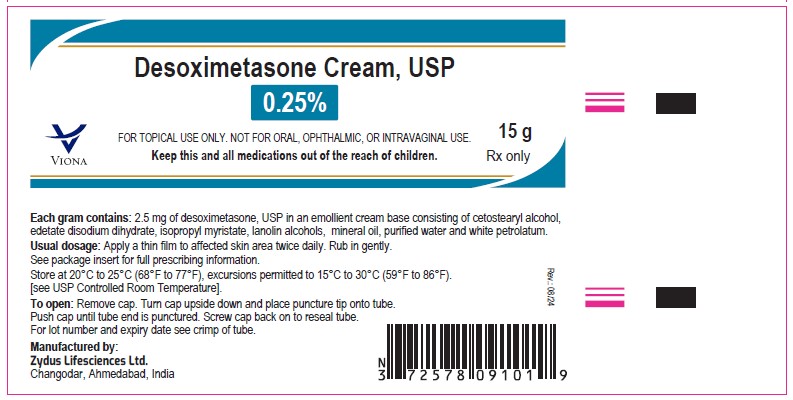 DRUG LABEL: desoximetasone
NDC: 70771-1437 | Form: CREAM
Manufacturer: Zydus Lifesciences Limited
Category: prescription | Type: HUMAN PRESCRIPTION DRUG LABEL
Date: 20240814

ACTIVE INGREDIENTS: DESOXIMETASONE 2.5 mg/1 g
INACTIVE INGREDIENTS: CETOSTEARYL ALCOHOL; EDETATE DISODIUM; ISOPROPYL MYRISTATE; LANOLIN ALCOHOLS; MINERAL OIL; WATER; PETROLATUM

Desoximetasone Cream USP, 0.25%

PACKAGE LABEL.PRINCIPAL DISPLAY PANEL

NDC 70771-1437-1 in tube of 15gm

Desoximetasone Cream USP, 0.25%

Rx only

15 gm